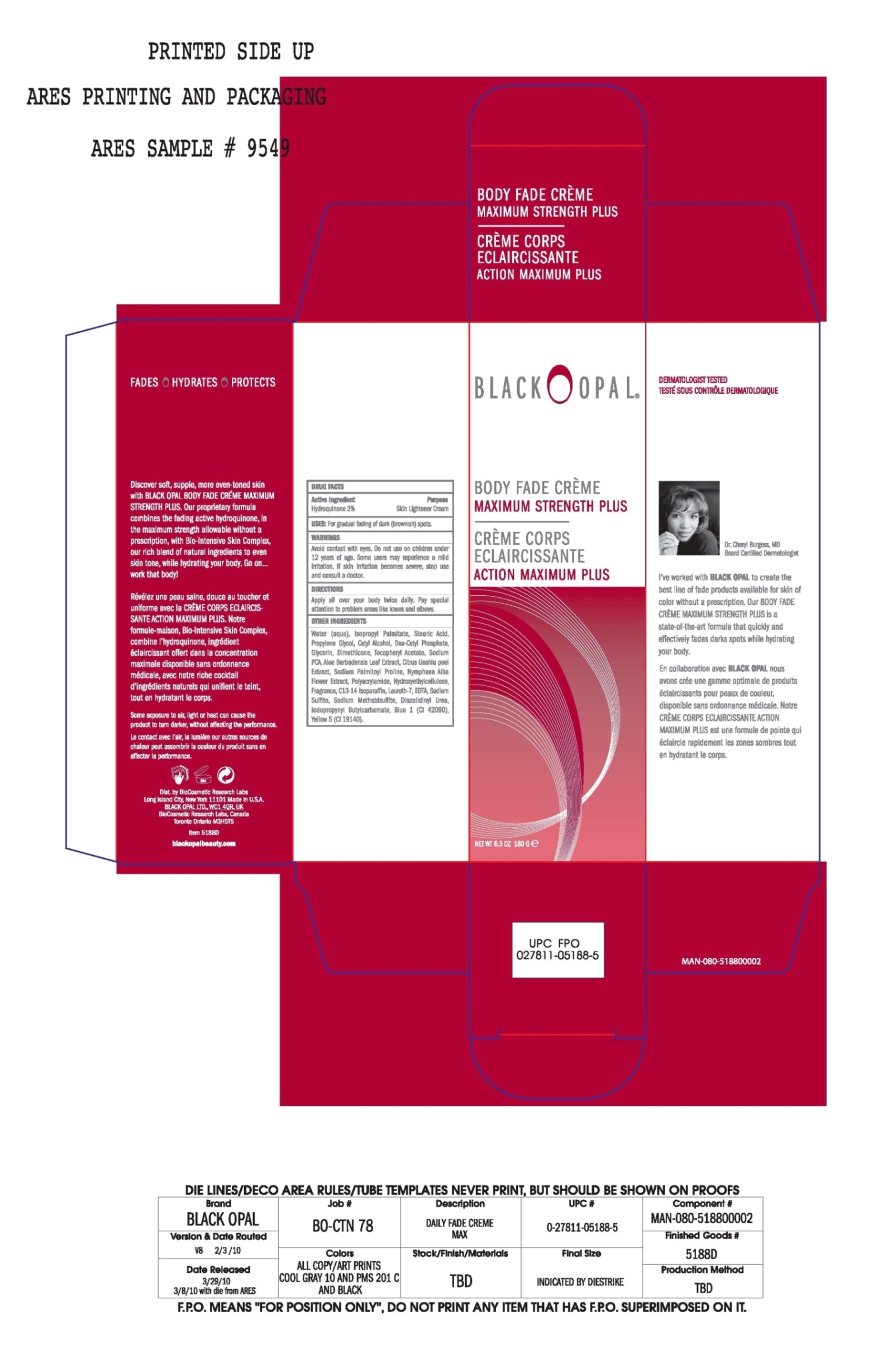 DRUG LABEL: Body Fade Creme
NDC: 59735-304 | Form: CREAM
Manufacturer: Biocosmetic Reasearch Labs
Category: otc | Type: HUMAN OTC DRUG LABEL
Date: 20091208

ACTIVE INGREDIENTS: Hydroquinone 2 g/100 g

Body Fade Creme Maximum Strength

Active Ingredient

Hydroquinone 2%

Purpose

Skin Lightener Cream

Uses

For gradual fading of dark (brownish) spots.

Warnings

Avoid contact with eyes.

Do not use on children under 12 years of age.

STOP USE

Some users may experience a mild irritation. If skin Irritation becomes severe, stop use and consult a doctor.

Directions

Apply all over your body twice daily. Pay special attention to problem areas like knees and elbows.

Inactive Ingredients

Water (Aqua), Isopropyl Palmitate, Stearic Acid, Propylene Glycol, Cetyl Alcohol, DEA-Cetyl Phosphate, glycerin, Dimethicone, Tocopheryl Acetate, Sodium PCA, Aloe Barbadensis Leaf Extract, Citrus Unshiu Peel Extract, Sodium Palmitoyl Proline, Nymphaea Alba Flower Extract, Polyacrylamide, Hydroxyethylcellulose, Fragrance, C13-14 Isoparaffin, Laureth-7, EDTA, Sodium Sulfite, Sodium Metabisulfite, Diazolidinyl Urea, Iodopropynyl Butylcarbamate, Blue 1 (CI 42090), Yellow 5 (CI 19140)